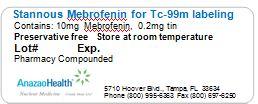 DRUG LABEL: Mebrofenin
NDC: 51808-216 | Form: INJECTION, POWDER, LYOPHILIZED, FOR SOLUTION
Manufacturer: AnazaoHealth Corporation
Category: prescription | Type: HUMAN PRESCRIPTION DRUG LABEL
Date: 20120619

ACTIVE INGREDIENTS: MEBROFENIN 10 mg/1 1
INACTIVE INGREDIENTS: STANNOUS CHLORIDE 0.2 mg/1 1

Mebrofenin

Dear Medical Professional,

Per your order, we have compounded Mebrofenin as a sterile solution. The characteristics of this preparation are

DESCRIPTION

AnazaoHealth supplies compounded Mebrofenin for the preparation of Tc-99m Mebrofenin. Each reaction vial contains 10 mg Mebrofenin and 0.2 mg tin as stannous chloride. The vial is back filled with nitrogen gas after lyophilization. The vial may contain a partial vacuum.

INDICATIONS AND USAGE

Technetium Tc-99m Mebrofenin by intravenous administration is indicated as a hepatic imaging agent, used in the diagnosis of liver disease

DOSAGE AND ADMINISTRATION

The suggested intravenous dose range of Technetium Tc 99m Mebrofenin in the average patient (70 kg) is:

Nonjaundiced patient: 74 - 185 MBq (2-5 mCi)

Patient with serum bilirubin level greater than 1.5 mg/dL: 111-370 MBq (3-10 mCi)

The patient should be in a fasting state, 4 hours is preferable. False positives (non-visualization) may result if the gallbladder has been emptied by ingestion of food.

An interval of at least 24 hours should be allowed before repeat examination

PREPARATION

To prepare injection, follow this aseptic procedure:

1. Waterproof gloves should be worn during the preparation procedure.
2. Snap off the plastic lid and place room temperature reaction vial in an appropriate lead shield.
3. Swab the rubber closure of the vial with a germicide.
4. Inject 1 – 3 ml Sterile additive free sodium pertechnetate Tc-99m injection containing up to 740 MBq (20 mCi) into the vial. Be sure to maintain inert atmosphere in vial by introducing as little air as possible during reconstitution. NOTE: If sodium pertechnetate Tc-99m injection must be diluted, use only preservative free Sodium Chloride Injection USP.
5. Secure the lead shield cover. Swirl the vial gently to mix contents and let stand 3 to 5 minutes prior to use.
6. Record the date and time of preparation on a pressure-sensitive label.
7. Affix pressure-sensitive label to shield.
8. Examine vial contents; if the solution is not clear and free of particulate matter and discoloration on visual inspection, it should not be used.
9. Measure the radioactivity by suitable calibration system and record prior to patient administration.
10. Appropriate quality control is recommended.
11. Use within 12 hours of preparation

PACKAGE LABEL.PRINCIPAL DISPLAY PANEL

Figure 1